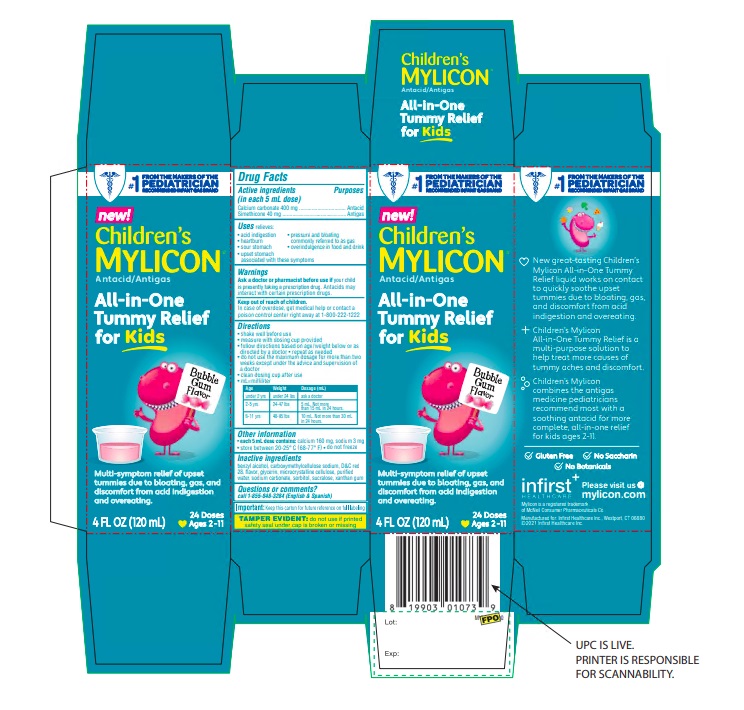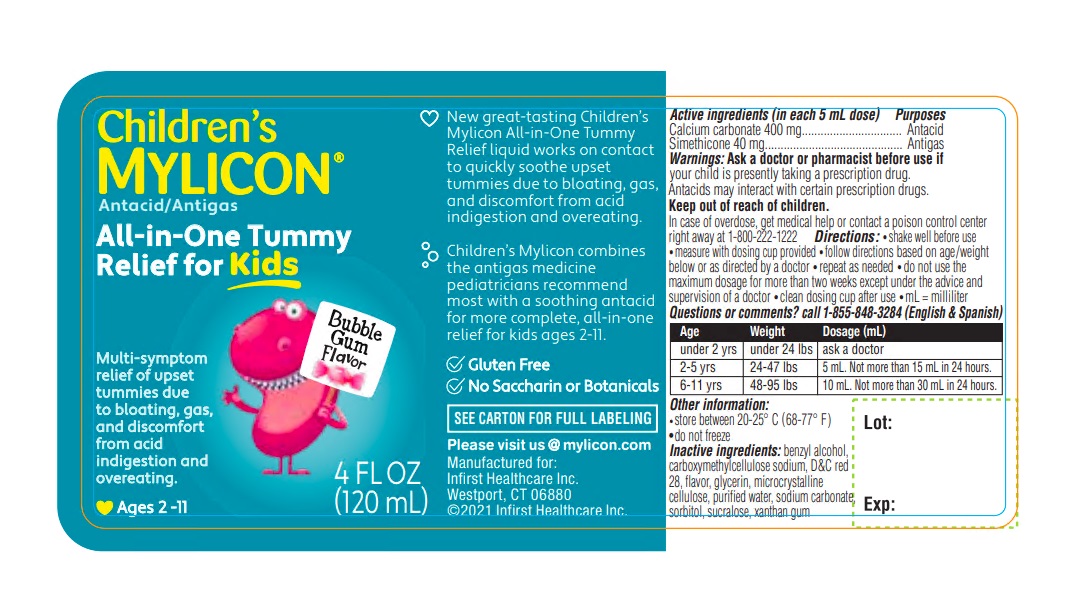 DRUG LABEL: Childrens Mylicon All in One Tummy Relief for Kids
NDC: 62372-410 | Form: LIQUID
Manufacturer: Infirst Healthcare Inc.
Category: otc | Type: HUMAN OTC DRUG LABEL
Date: 20240101

ACTIVE INGREDIENTS: CALCIUM CARBONATE 400 mg/5 mL; DIMETHICONE 40 mg/5 mL
INACTIVE INGREDIENTS: BENZYL ALCOHOL; CARBOXYMETHYLCELLULOSE SODIUM, UNSPECIFIED; D&C RED NO. 28; GLYCERIN; MICROCRYSTALLINE CELLULOSE; WATER; SODIUM CARBONATE; SORBITOL; SUCRALOSE; XANTHAN GUM

Children’s Mylicon All-in-One Tummy Relief for Kids

Active ingredients (in each 5 mL dose)

Calcium carbonate 400 mg

Simethicone 40 mg

Purpose

Antacid

Antigas

Uses

relieves:

- acid indigestion
- heartburn
- sour stomach
- upset stomach associated with these symptoms
- pressure and bloating commonly referred to as gas
- overindulgence in food and drink

Warnings

Ask a doctor or pharmacist before use if

your child is presently taking a prescription drug. Antacids may interact with certain prescription drugs.

Keep out of reach of children.

In case of overdose, get medical help or contact a poison control center right away at 1-800-222-1222

Directions

- shake well before use
- measure with dosing cup provided
- follow directions based on age/weight below or as directed by a doctor
- repeat as needed
- do not use the maximum dosage for more than two weeks except under the advice and supervision of a doctor
- clean dosing cup after use
- mL = milliliter

Age | Weight | Dosage (mL)
under 2 yrs | under 24 lbs | ask a doctor
2-5 yrs | 24-47 lbs | 5 mL. Not more than 15 mL in 24 hours.
6-11 yrs | 48-95 lbs | 10 mL. Not more than 30 mL in 24 hours.

Other information

- each 5 mL dose contains:calcium 160 mg, sodium 3 mg
- store between 20-25°C (68-77°F)
- do not freeze

Inactive ingredients

benzyl alcohol, carboxymethylcellulose sodium, D&C red 28, flavor, glycerin, microcrystalline cellulose, purified water, sodium carbonate, sorbitol, sucralose, xanthan gum

Questions or comments?

call 1-855-848-3284 (English & Spanish)

Package/Label Principal Display Panel

FROM THE MAKERS OF THE #1 PEDIATRICIAN RECOMMENDED INFANT GAS BRAND

new!

Children’s MYLICON®

Antacid/Antigas

All-in-One Tummy Relief for Kids

Multi-symptom relief of upset tummies due to bloating, gas, and discomfort from acid indigestion and overeating.

Bubble Gum Flavor

4 FL OZ (120 mL) 24 Doses
Ages 2-11

Important:Keep this carton for future reference on full labeling

TAMPER EVIDENT:do not use if printed safety seal under cap is broken or missing

New great-tasting Children’s Mylicon All-in-One Tummy Relief liquid works on contact to quickly soothe upset tummies due to bloating, gas, and discomfort from acid indigestion and overeating.

Children’s Mylicon All-in-One Tummy Relief is a multi-purpose solution to help treat more causes of tummy aches and discomfort..

Children’s Mylicon combines the antigas medicine pediatricians recommend most with a soothing antacid for more complete, all-in-one relief for kids ages 2-11.

Gluten Free

No Saccharin

No Botanicals

Please visit us @ mylicon.com

Manufactured for: Infirst Healthcare Inc., Westport, CT 06880

©2021 Infirst Healthcare Inc.

Children’s MYLICON®

Antacid/Antigas

All-in-One Tummy Relief for Kids

Multi-symptom relief of upset tummies due to bloating, gas, and discomfort from acid indigestion and overeating.

Bubble Gum Flavor

Ages 2-11

4 FL OZ (120 mL)

New great-tasting Children’s Mylicon All-in-One Tummy Relief liquid works on contact to quickly soothe upset tummies due to bloating, gas, and discomfort from acid indigestion and overeating.

Children’s Mylicon combines the antigas medicine pediatricians recommend most with a soothing antacid for more complete, all-in-one relief for kids ages 2-11.

Gluten Free

No Saccharin or Botanicals

SEE CARTON FOR FULL LABELING

Please visit us @ mylicon.com

Manufactured for:

Infirst Healthcare Inc.

Westport, CT 06880

©2021 Infirst Healthcare Inc.